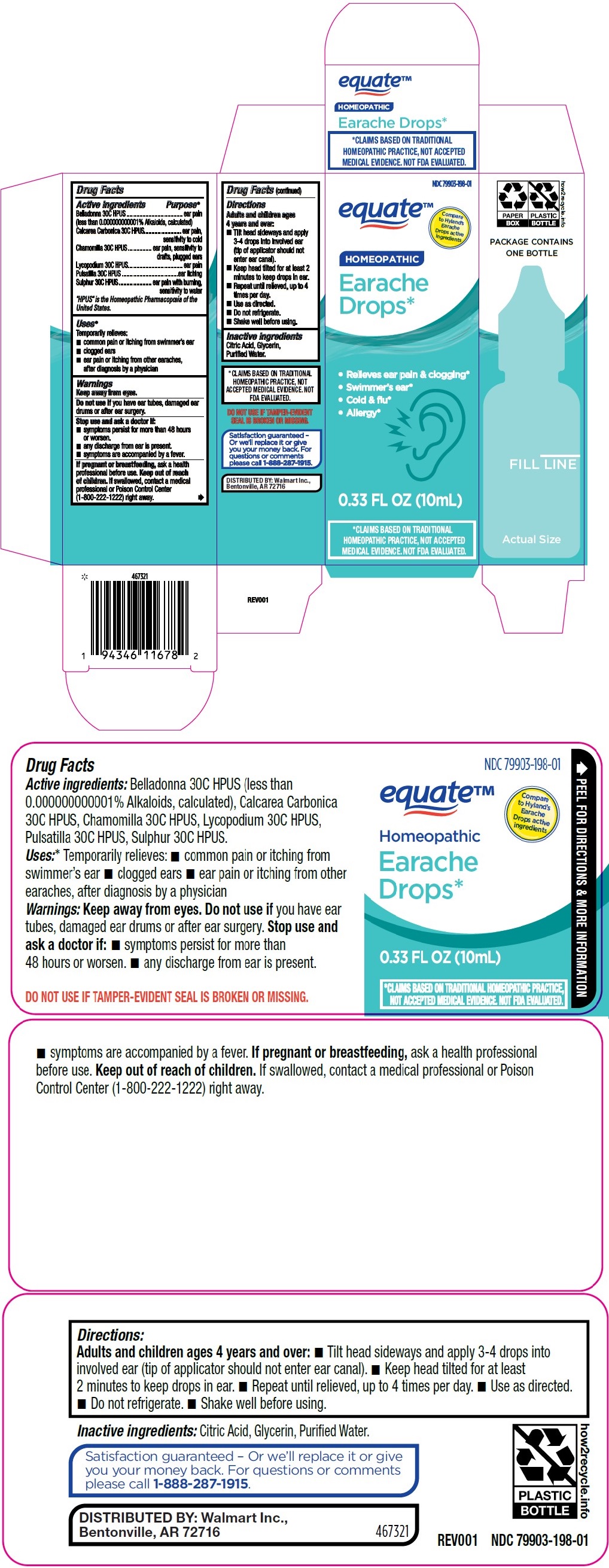 DRUG LABEL: Equate Homeopathic Earache Drops
NDC: 79903-198 | Form: LIQUID
Manufacturer: Walmart Inc.
Category: homeopathic | Type: HUMAN OTC DRUG LABEL
Date: 20230705

ACTIVE INGREDIENTS: CHAMOMILE 30 [hp_C]/1 mL; ANEMONE PATENS WHOLE 30 [hp_C]/1 mL; CALCIUM CARBONATE 30 [hp_C]/1 mL; BELLADONNA LEAF 30 [hp_C]/1 mL; LYCOPODIUM CLAVATUM SPORE 30 [hp_C]/1 mL; SULFUR 30 [hp_C]/1 mL
INACTIVE INGREDIENTS: GLYCERIN; WATER; CITRIC ACID MONOHYDRATE

Equate Homeopathic Earache Drops

Drug Facts

Active ingredients | Purpose*
Belladonna 30C HPUS; (less than 0.000000000001% Alkaloids, calculated) | ear pain
Calcarea Carbonica 30C HPUS | ear pain, sensitivity to cold
Chamomilla 30C HPUS | ear pain, sensitivity to drafts, plugged ears
Lycopodium 30C HPUS | ear pain
Pulsatilla 30C HPUS | ear itching
Sulphur 30C HPUS | ear pain with burning, sensitivity to water

"HPUS" is the Homeopathic Pharmacopœia of the United States.

Uses*

Temporarily relieves:

■common pain or itching from swimmer’s ear
■clogged ears
■ear pain or itching from other earaches, after diagnosis by a physician

Warnings

Keep away from eyes.

Do not use if you have ear tubes, damaged ear drums or after ear surgery.

Stop use and ask a doctor if:

■ symptoms persist for more than 48 hours or worsen.
■ any discharge from ear is present.
■ symptoms are accompanied by a fever.

PREGNANCY OR BREAST FEEDING

If pregnant or breastfeeding, ask a health professional before use.

Keep out of reach of children. If swallowed, contact a medical professional or Poison Control Center (1-800-222-1222) right away.

Drug Facts (continued)

Directions

Adults and children ages 4 years and over:

■ Tilt head sideways and apply 3-4 drops into involved ear (tip of applicator should not enter ear canal).
■ Keep head tilted for at least 2 minutes to keep drops in ear.
■ Repeat until relieved, up to 4 times per day.
■ Use as directed.
■ Do not refrigerate.
■ Shake well before using.

Inactive ingredients

Citric Acid, Glycerin, Purified Water.

QUESTIONS

1-888-287-1915

DISTRIBUTED BY: Walmart Inc., Bentonville, AR 72716

PURPOSE

Temporarily relieves common pain or itching from swimmer’s ear, clogged ears, ear pain or itching from other earaches, after diagnosis by a physician

Principal Display Panel

NDC 79903-198-01

equate™

Compare

to Hyland's

Earache

Drops active

ingredients

HOMEOPATHIC

Earache

Drops*

- Relieves ear pain & clogging*
- Swimmer's ear*
- Cold & flu*
- Allergy*

0.33 FL OZ (10mL)

*CLAIMS BASED ON TRADITIONAL
HOMEOPATHIC PRACTICE, NOT
ACCEPTED MEDICAL EVIDENCE. NOT
FDA EVALUATED.